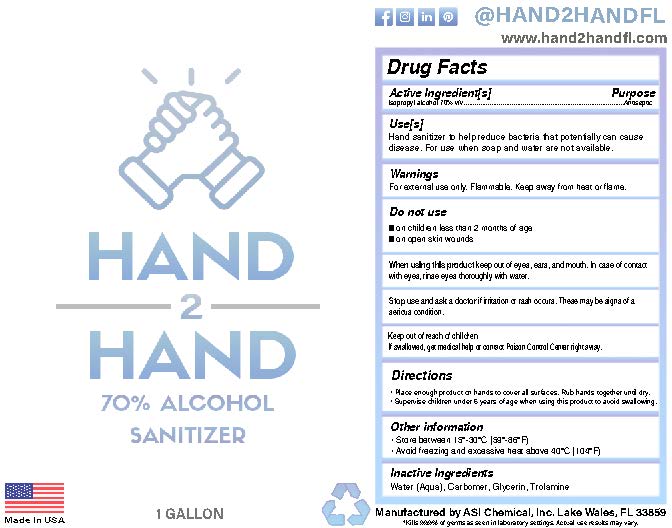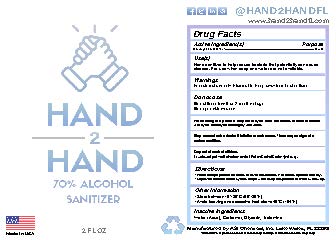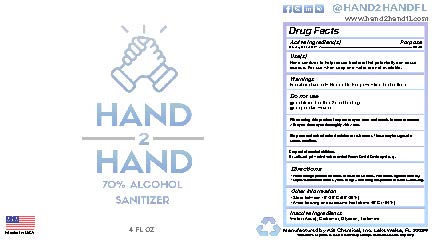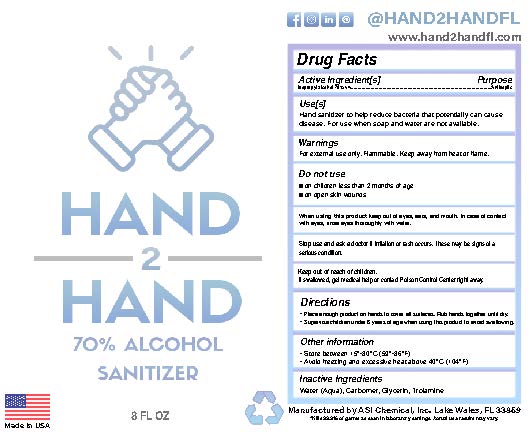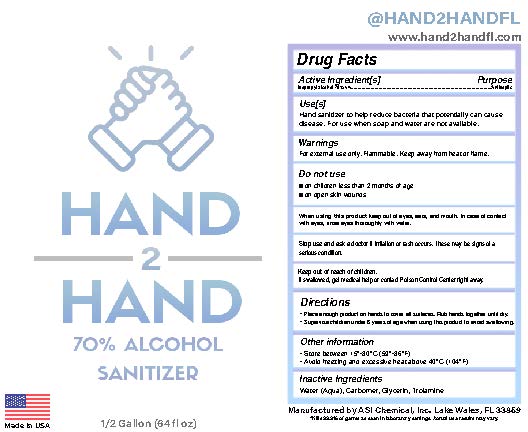 DRUG LABEL: Hand 2 Hand Sanitizer
NDC: 78437-100 | Form: GEL
Manufacturer: ASI Chemical, Inc.
Category: otc | Type: HUMAN OTC DRUG LABEL
Date: 20211214

ACTIVE INGREDIENTS: ISOPROPYL ALCOHOL 42 mL/60 mL
INACTIVE INGREDIENTS: CARBOMER 940; TROLAMINE; WATER; GLYCERIN

Hand 2 Hand Sanitizer

Active Ingredient

Isopropyl Alcohol 70%

Purpose

Antiseptic

Uses

Hand Sanitizer to help reduce bacteria that potentially can cause disease. For use when soap and water are not available.

Warnings

For External Use Only. FLAMMABLE. Keep away from heat or flame

Do not use with children less than 2 months of age. On open wounds or broken skin.

When using this product

keep out of eyes, ears, and mouth. In case of contact with eyes, rinse eyes thoroughly with water.

Stop use and ask a doctor if irritation or rash occurs. These may be signs of a serious condition

Keep out of reach of children.

If swallowed, get medical help or contact a Poison Control Center right away.

Directions

Place enough product on hands to cover all surfaces. Rub hands together until dry. Supervise children under 6 years of age when using this product to avoid swallowing

Other Information

Store between 15-30C (59-86F). -Avoid freezing and temperatures above 40C (104F).

Inactive Ingredients

Water (Aqua), Carbomer, Glycerin, Trolamine